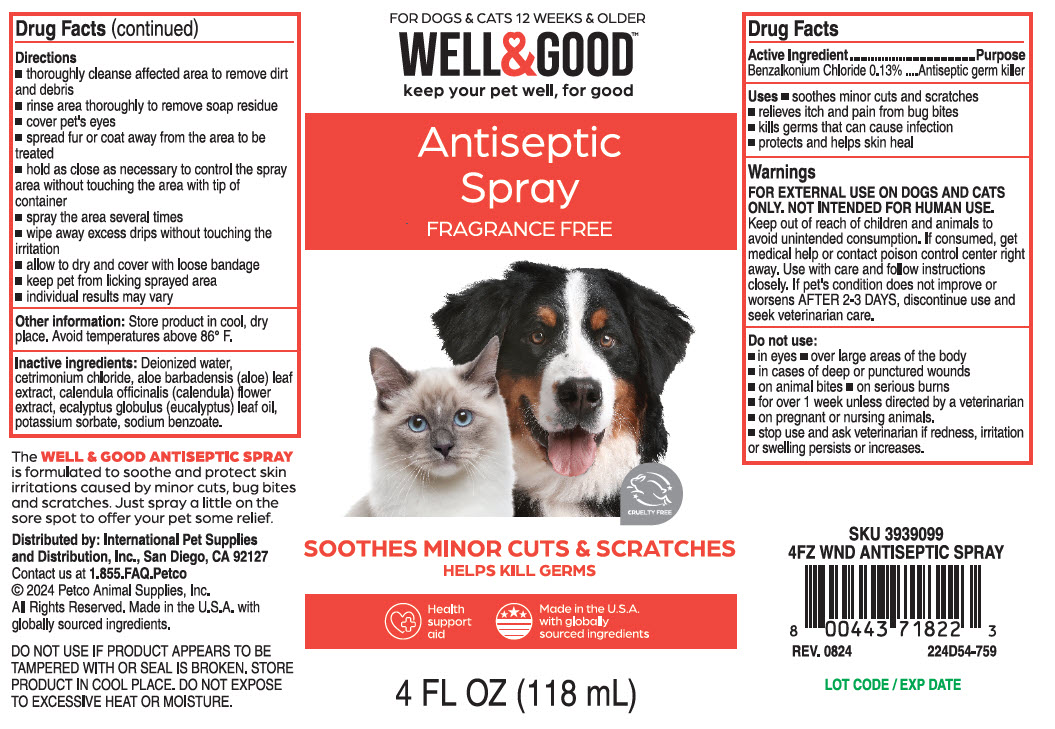 DRUG LABEL: Well and Good
NDC: 27102-541 | Form: SPRAY
Manufacturer: International Pet Supplies & Distrubtion
Category: animal | Type: OTC ANIMAL DRUG LABEL
Date: 20240930

ACTIVE INGREDIENTS: BENZALKONIUM CHLORIDE 1.3 g/118 mL

Antiseptic Spray

Warning

FOR EXTERNAL USE ON DOGS AND CATS ONLY. NOT INTENDED FOR HUMAN USE. Keep out of reach of children and animals to avoid unintended consumption. If consumed, get medical help or contact poison control center right away. Use with care and follow instructions closely. If pet's condition does not improve or worsens AFTER 2-3 DAYS, discontinue use and seek veterinarian care.

Directions

- Thoroughly cleanse affected area to remove dirt and debris.
- Rinse area thoroughly to remove soap residue.
- Cover pet's eyes.
- Spread fur or coat away from the area to be treated.
- Hold as close as necessary to control the spray area without touching the area with tip of container.
- Spray the area several times.
- Wipe away excess drips without touching the irritation.
- Allow to dry and cover with loose bandage
- Keep pet from licking sprayed area
- Individual results may vary.